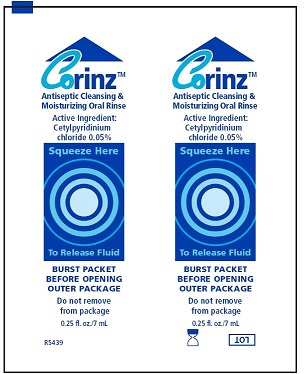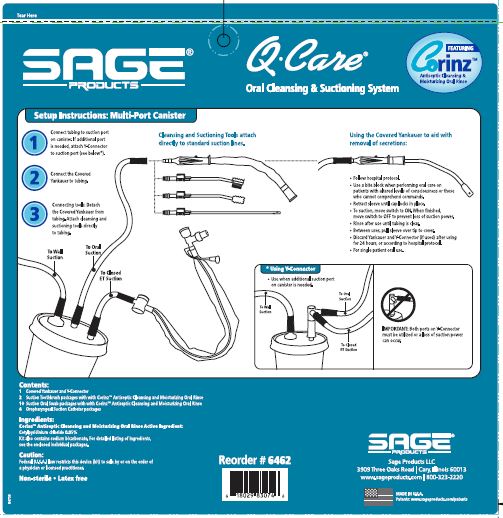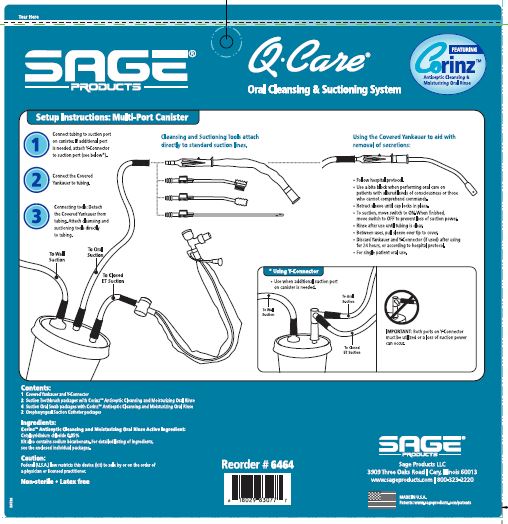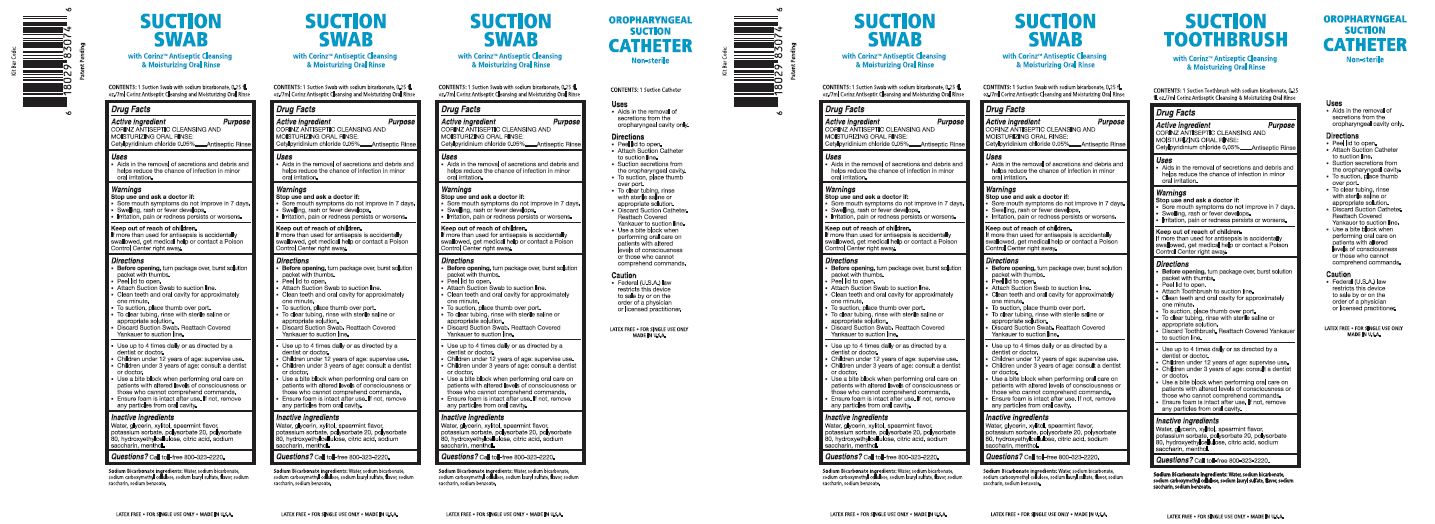 DRUG LABEL: QCARE ORAL CLEANSING AND SUCTIONING SYSTEM
NDC: 53462-462 | Form: KIT | Route: BUCCAL
Manufacturer: Sage Products LLC
Category: otc | Type: HUMAN OTC DRUG LABEL
Date: 20160129

ACTIVE INGREDIENTS: CETYLPYRIDINIUM CHLORIDE .5 mg/1 mL
INACTIVE INGREDIENTS: WATER; GLYCERIN; XYLITOL; POTASSIUM SORBATE; POLYSORBATE 20; POLYSORBATE 80; HYDROXYETHYL CELLULOSE (4000 MPA.S AT 1%); CITRIC ACID MONOHYDRATE; SACCHARIN SODIUM; MENTHOL, UNSPECIFIED FORM

QCare Oral Cleansing & Suctioning System Corinz™ Antiseptic Cleansing and Moisturizing Oral Rinse

Drug Facts

Active ingredient: | Purpose
Corinz™ Antiseptic Cleansing and Moisturizing Oral Rinse:
Cetylpyridinium chloride 0.05% | Antiseptic Rinse

Uses

- Aids in the removal of secretions and debris and helps reduce the chance of infection in minor oral irritation.

Oropharyngeal Suction Catheter Non-sterile

- Aids in the removal of secretions from the oropharyngeal cavity only.

Warnings

Stop use and ask a doctor if:
- Sore mouth symptoms do not improve in 7 days.
- Swelling, rash or fever develops.
- Irritation, pain or redness persists or worsens.

Keep out of reach of children.
If more than used for antisepsis is accidentally swallowed, get medical help or contact a Poison Control Center right away.

Directions

Toothette Oral Care Suction Toothbrush
- Before opening, turn package over, burst solution packet with thumbs.
- Peel lid to open.
- Attach Toothbrush to suction line.
- Clean teeth and oral cavity for approximately one minute.
- To suction, place thumb over port.
- To clear tubing, rinse with sterile saline or appropriate solution.
- Discard Toothbrush. Reattach Covered Yankauer to suction line.

- Use up to 4 times daily or as directed by a dentist or doctor.
- Children under 12 years of age: supervise use.
- Children under 3 years of age: consult a dentist or doctor.
- Use a bite block when performing oral care on patients with altered levels of consciousness or those who cannot comprehend commands.
- Ensure foam is intact after use. If not, remove any particles from oral cavity.

Toothette Oral Care Suction Swab
- Before opening, turn package over, burst solution packet with thumbs.
- Peel lid to open.
- Attach Suction Swab to suction line.
- Clean teeth and oral cavity for approximately one minute.
- To suction, place thumb over port.
- To clear tubing, rinse with sterile saline or appropriate solution.
- Discard Suction Swab. Reattach Covered Yankauer to suction line.

- Use up to 4 times daily or as directed by a dentist or doctor.
- Children under 12 years of age: supervise use.
- Children under 3 years of age: consult a dentist or doctor.
- Use a bite block when performing oral care on patients with altered levels of consciousness or those who cannot comprehend commands.
- Ensure foam is intact after use. If not, remove any particles from oral cavity.

Oropharyngeal Suction Catheter Non-sterile
- Peel lid to open.
- Attach Suction Catheter to suction line.
- Suction secretions from the oropharyngeal cavity.
- To suction, place thumb over port.
- To clear tubing, rinse with sterile saline or appropriate solution.
- Discard Suction Catheter. Reattach Covered Yankaurer to suction line.
- Use a bite block when performing oral care on patients with altered levels of consciousness or those who cannot comprehend commands.

Inactive ingredients

Water, glycerin, xylitol, spearmint flavor, potassium sorbate, polysorbate 20, polysorbate 80, hydroxyethylcellulose, citric acid, sodium saccharin, menthol.

Questions?

Call toll-free 800-323-2220.

LATEX FREE FOR SINGLE USE ONLY MADE IN U.S.A.

Corinz Label

PACKAGE LABEL

QCARE ORAL CLEANSING AND SUCTIONING SYSTEM